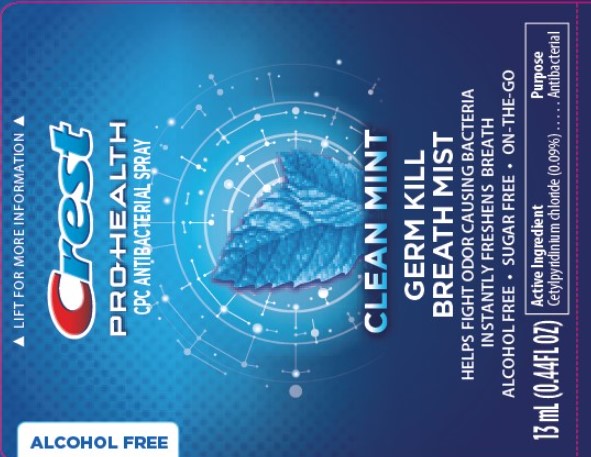 DRUG LABEL: CPH Anti-bacterial Breath Mist
NDC: 63645-179 | Form: SPRAY
Manufacturer: OraLabs
Category: otc | Type: HUMAN OTC DRUG LABEL
Date: 20250422

ACTIVE INGREDIENTS: CETYLPYRIDINIUM CHLORIDE 1.11 g/13 mL
INACTIVE INGREDIENTS: WATER 11.18 mL/13 mL; HYDROGENATED CASTOR OIL 1.3 mL/13 mL; MENTHOL, (+)- 0.0065 mL/13 mL; SUCRALOSE 0.039 mL/13 mL

Drug Facts

Active ingredient

Cetylpyridinium chloride 0.09%

Purpose

Antibacterial

Keep Out of Reach of Children

If swallowed get medical help or contact a Poison Control Center right away.

Uses

Helps fight odor causing bacteria

Warnings

For external use only:

Do not use this product if gums are irritated or bleeding unless directed to do by a doctor or dentist. If more than twice the recommended amount for tongue spraying is accidentally swallowed, get medical help or contact a Poison Control Center immediately. Do not spray into the eyes. Do not spray into the eyes. If spray gets into the eyes, hold eyelids apart and flush the eye continuously with running water for at least 15 minutes.

Directions

Adults and children 12 years of age and older: Spray 3 times in the oral cavity. Children 6-12 years of age: Supervise use. Children under 6 years: Do not use.

Inactive Ingredients

Citric Acid, Flavor, Glycerin, Menthol, PEG-40 Hydrogenated Castor Oil, Potassium Sorbate, Sodium Benzoate, Sucralose, Water.